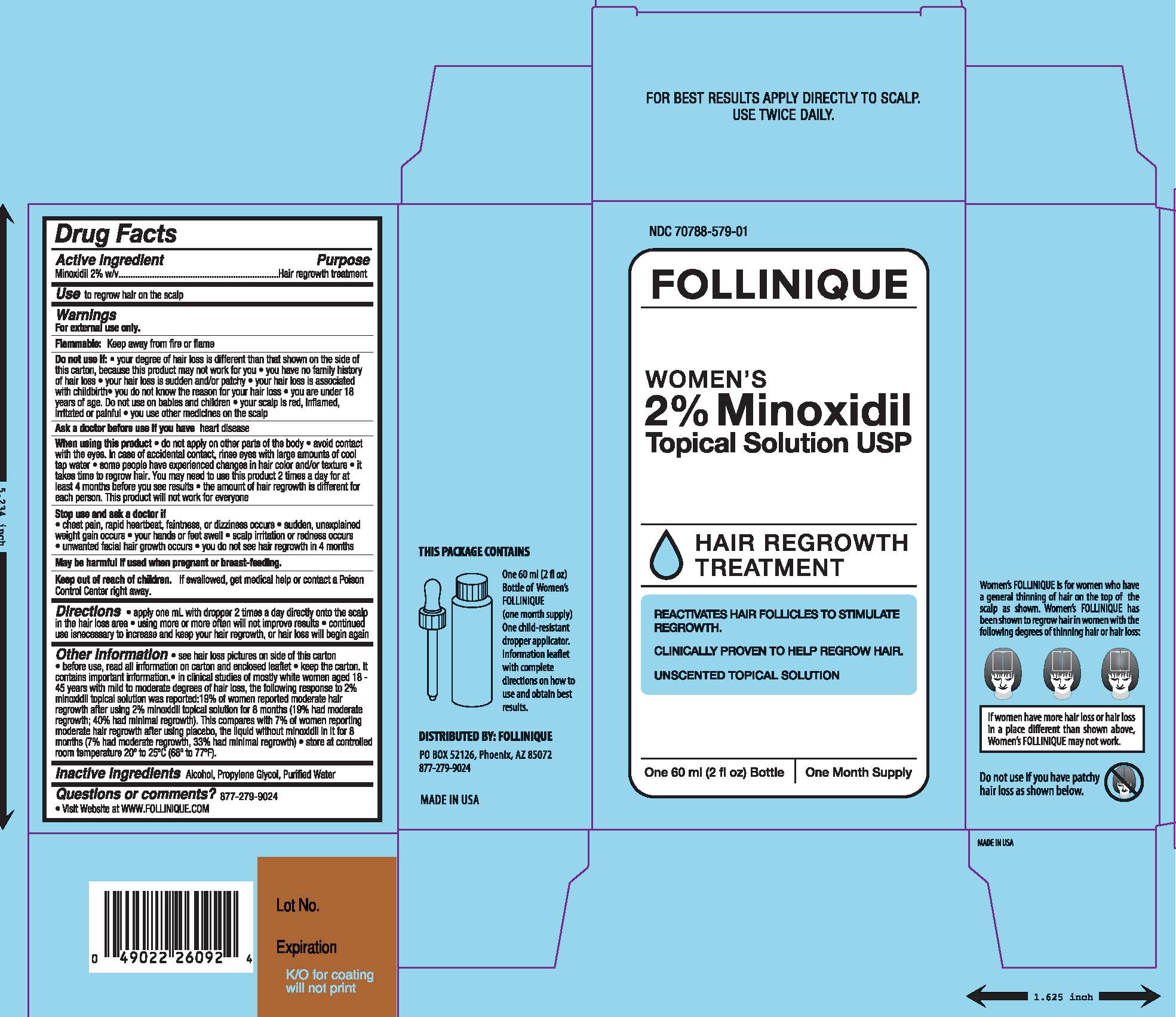 DRUG LABEL: Follinique
NDC: 70788-579 | Form: SOLUTION
Manufacturer: Premium Distribution, LLC
Category: otc | Type: HUMAN OTC DRUG LABEL
Date: 20170427

ACTIVE INGREDIENTS: MINOXIDIL 20 mg/1 mL
INACTIVE INGREDIENTS: WATER; PROPYLENE GLYCOL; ALCOHOL

Follinique

Active ingredients:

Minoxidil 2.0% w/v

Purpose

Hair regrowth treatment

Use

to regrow hair on the scalp

Warnings

For external use only.
Flammable: Keep away from fire or flame

Do not use if

- your degree of hair loss is different than that shown on the side of this carton, because this product may not work for you
- you have no family history of hair loss
- your hair loss is sudden and/or patchy
- your hair loss is associated with childbirth
- you do not know the reason for your hair loss
- you are under 18 years of age. Do not use on babies and children.
- your scalp is red, inflamed, infected, irritated, or painful
- you use other medications on the scalp

Ask a doctor before use if you have heart disease.

When using this product

- do not apply on other parts of the body
- avoid contact with the eyes. In case of accidental contact, rinse eyes with large amounts of cool tap waler.
- some people have experienced changes in hair color and/or texture
- it takes time to regrow hair. You may need to use this product 2 times a day at least 4 months before you see results
- the amount of hair regrowth is different for each person. This product will not work for everyone

Stop use and ask a doctor if

- chest pain, rapid heartbeat, faintness, or dizziness occurs
- sudden, unexplained weight gain occurs
- your hands or feet swell
- scalp irritation or redness occurs
- unwanted facial hair growth occurs
- you do not see hair regrowth in 4 months

PREGNANCY OR BREAST FEEDING

If pregnant or breast feeding, ask a health professional before use.

Keep out of reach of children.
If swallowed, get medical help or contact a Poison Control Center right away.

Directions

- apply one mL with dropper 2 times a day directly onto the scalp in the hair loss area
- using more or more often will not improve results
- continued use is necessary to increase and keep your hair regrowth, or hair loss will begin again

Other Information

- see hair loss pictures on side of this carton
- before use, read all information on carton and enclosed leaflet
- in clinical research in mostly white women age 18-45 years with mild to moderate degrees of hair loss, the following response to Minoxidil Topical Solution 2% was reported: 19% of women reported moderate hair regrowth after using women's Minoxidil Topical Solution 2% for 8 months; 19% had moderate regrowth; 40% had minimal regrowth. This compares with 7% of women reporting hair regrowth after using the placebo, the liquid without Minoxidil in it, for 8 months (7% had moderate regrowth, 33% had minimal regrowth)
- keep the carton. It contains important information.
- store at controlled room temperature 20^0 to 25^0C (68^0 to 77^0F).

Inactive Ingredients:

alcohol , propylene glycol, purified water.

Questions or comments?

877-279-9024

Visit website at www.follinique.com

PACKAGE LABEL

NDC 70788-579-01

Follinique

Women's 2% Minoxidil Topical Solution USP

Hair Regrowth Treatment

Reactivates Hair Follicles to Stimulate Regrowth

Clinically Proven to Help Regrow Hair

Unscented Topical Solution